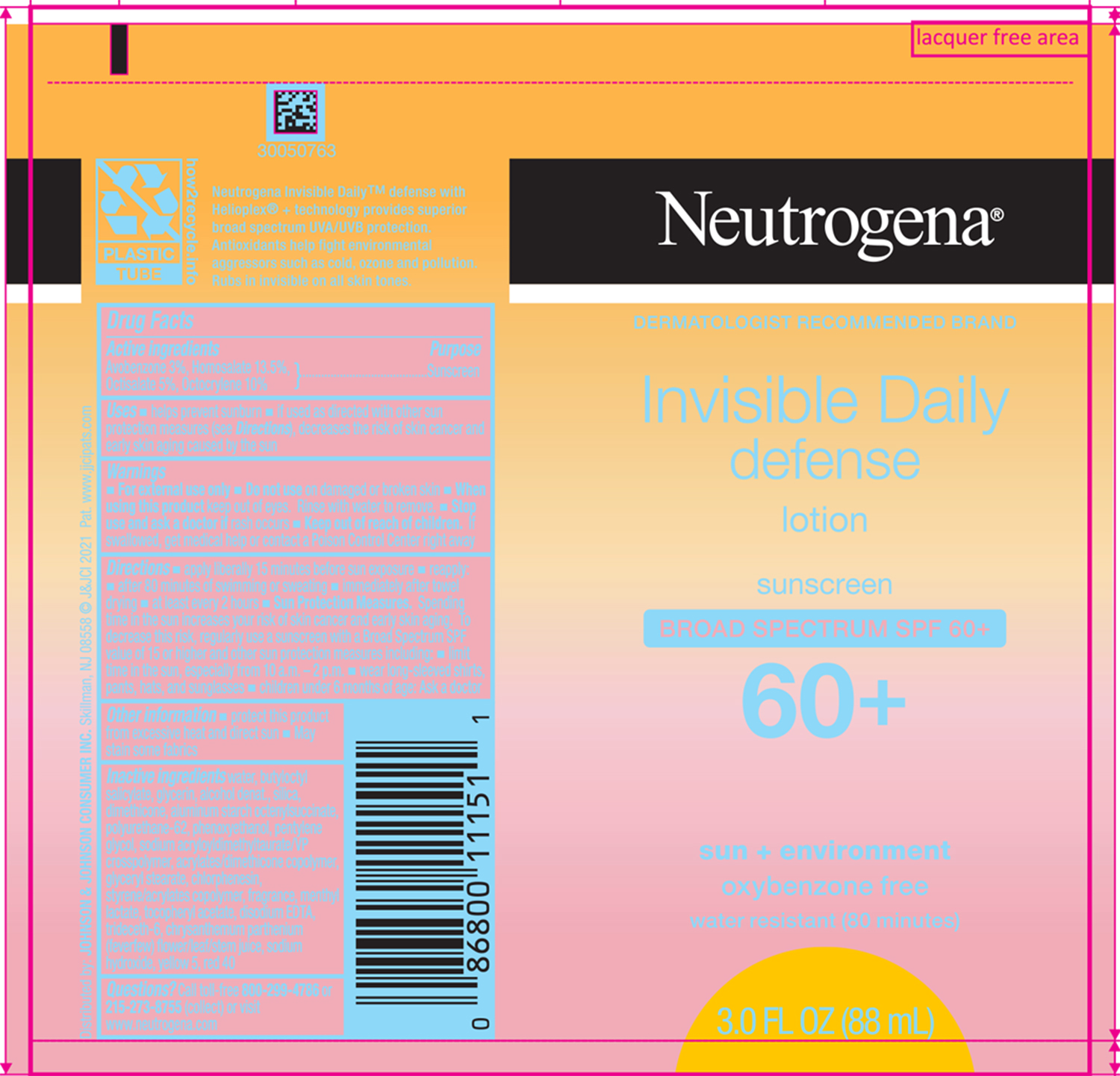 DRUG LABEL: Neutrogena Invisible Daily Defense Sunscreen Broad Spectrum SPF 60 Plus
NDC: 69968-0661 | Form: LOTION
Manufacturer: Kenvue Brands LLC
Category: otc | Type: HUMAN OTC DRUG LABEL
Date: 20251008

ACTIVE INGREDIENTS: AVOBENZONE 30 mg/1 mL; HOMOSALATE 135 mg/1 mL; OCTISALATE 50 mg/1 mL; OCTOCRYLENE 100 mg/1 mL
INACTIVE INGREDIENTS: WATER; BUTYLOCTYL SALICYLATE; GLYCERIN; ALCOHOL; SILICON DIOXIDE; DIMETHICONE; ALUMINUM STARCH OCTENYLSUCCINATE; PHENOXYETHANOL; PENTYLENE GLYCOL; BUTYL METHACRYLATE/METHYL METHACRYLATE/METHACRYLIC ACID/STYRENE CROSSPOLYMER; GLYCERYL MONOSTEARATE; CHLORPHENESIN; MENTHYL LACTATE, (-)-; .ALPHA.-TOCOPHEROL ACETATE; EDETATE DISODIUM; TRIDECETH-6; FEVERFEW; SODIUM HYDROXIDE; FD&C YELLOW NO. 5; FD&C RED NO. 40; POLYURETHANE-62; 2-ETHYLHEXYL ACRYLATE, METHACRYLATE, METHYL METHACRYLATE, OR BUTYL METHACRYLATE/HYDROXYPROPYL DIMETHICONE COPOLYMER (30000-300000 MW)

Neutrogena® Invisible Daily defense lotion sunscreen BROAD SPECTRUM SPF 60+

Drug Facts

ACTIVE INGREDIENT

Active ingredients | Purpose
Avobenzone 3% | Sunscreen
Homosalate 13.5% | Sunscreen
Octisalate 5% | Sunscreen
Octocrylene 10% | Sunscreen

Uses

- helps prevent sunburn
- if used as directed with other sun protection measures (see Directions), decreases the risk of skin cancer and early skin aging caused by the sun

Warnings

- For external use only

- Do not use on damaged or broken skin

- When using this product keep out of eyes. Rinse with water to remove.

- Stop use and ask a doctor if rash occurs

- Keep out of reach of children. If swallowed, get medical help or contact a Poison Control Center right away

Directions

- apply liberally 15 minutes before sun exposure
- reapply:
  - after 80 minutes of swimming or sweating
  - immediately after towel drying
  - at least every 2 hours
- Sun Protection Measures. Spending time in the sun increases your risk of skin cancer and early skin aging. To decrease this risk, regularly use a sunscreen with a Broad Spectrum SPF value of 15 or higher and other sun protection measures including:
  - limit time in the sun, especially from 10 a.m. - 2 p.m.
  - wear long-sleeved shirts, pants, hats and sunglasses
  - Children under 6 months of age: Ask a doctor

Other information

- protect this product from excessive heat and direct sun
- may stain some fabrics

Inactive ingredients

water, butyloctyl salicylate, glycerin, alcohol denat., silica, dimethicone, aluminum starch octenylsuccinate, polyurethane-62, phenoxyethanol, pentylene glycol, sodium acryloyldimethyltaurate/VP crosspolymer, acrylates/dimethicone copolymer, glyceryl stearate, chlorphenesin, styrene/acrylates copolymer, fragrance, menthyl lactate, tocopheryl acetate, disodium EDTA, trideceth-6, chrysanthemum parthenium (feverfew) flower/leaf/stem juice, sodium hydroxide, yellow 5, red 40

Questions?

Call toll-free 800-299-4786 or 215-273-8755 (collect) or visit www.neutrogena.com

Distributed by: JOHNSON & JOHNSON CONSUMER INC. Skillman, NJ 08558

PRINCIPAL DISPLAY PANEL - 88 mL Tube Label

Neutrogena®
DERMATOLOGIST RECOMMENDED BRAND

Invisible Daily
defense
lotion

sunscreen
BROAD SPECTRUM SPF 60+
60+

sun + environment
oxybenzone free
water resistant (80 minutes)

3.0 FL OZ (88 mL)